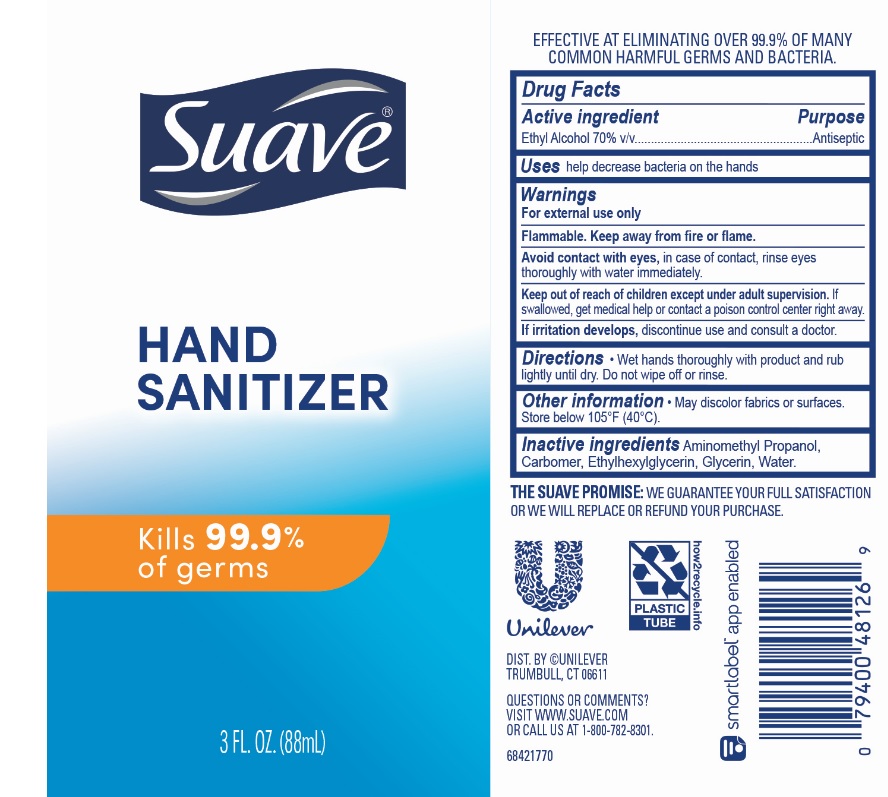 DRUG LABEL: Suave
NDC: 64942-1744 | Form: GEL
Manufacturer: Conopco Inc. d/b/a/ Unilever
Category: otc | Type: HUMAN OTC DRUG LABEL
Date: 20221207

ACTIVE INGREDIENTS: ALCOHOL 700 mg/1 mL
INACTIVE INGREDIENTS: WATER; GLYCERIN; CARBOMER HOMOPOLYMER, UNSPECIFIED TYPE; AMINOMETHYLPROPANOL; ETHYLHEXYLGLYCERIN

Suave Hand Sanitizer

SUAVE HAND SANITIZER - Ethyl Alcohol gel

Suave Hand Sanitizer

Drug Facts

Active ingredient

Ethyl Alcohol 70.0%

Purpose

Antiseptic

Uses

help decrease bacteria on the hands

Warnings

• For external use only
• Flammable. Keep away from fire or flame
• Avoid contact with eyes, in case of contact, rinse eyes thoroughly with water immediately.
• If irritation develps, discontinue use and consult a doctor.

• Keep out of reach of children except under adult supervision.

If swallowed, get medical help or contact a poison control Center right away.

Directions

Wet hands thoroughly with product and rub lightly until dry. Do not wipe off or rinse.

Other information

May discolor fabrics or surfaces. Store below 105˚F (40˚C).

Inactive ingredients

Aminomethyl Propanol, Carbomer, Ethylhexylglycerin, Glycerin, Water.

Questions?

Call us at 1-800-782-8301.